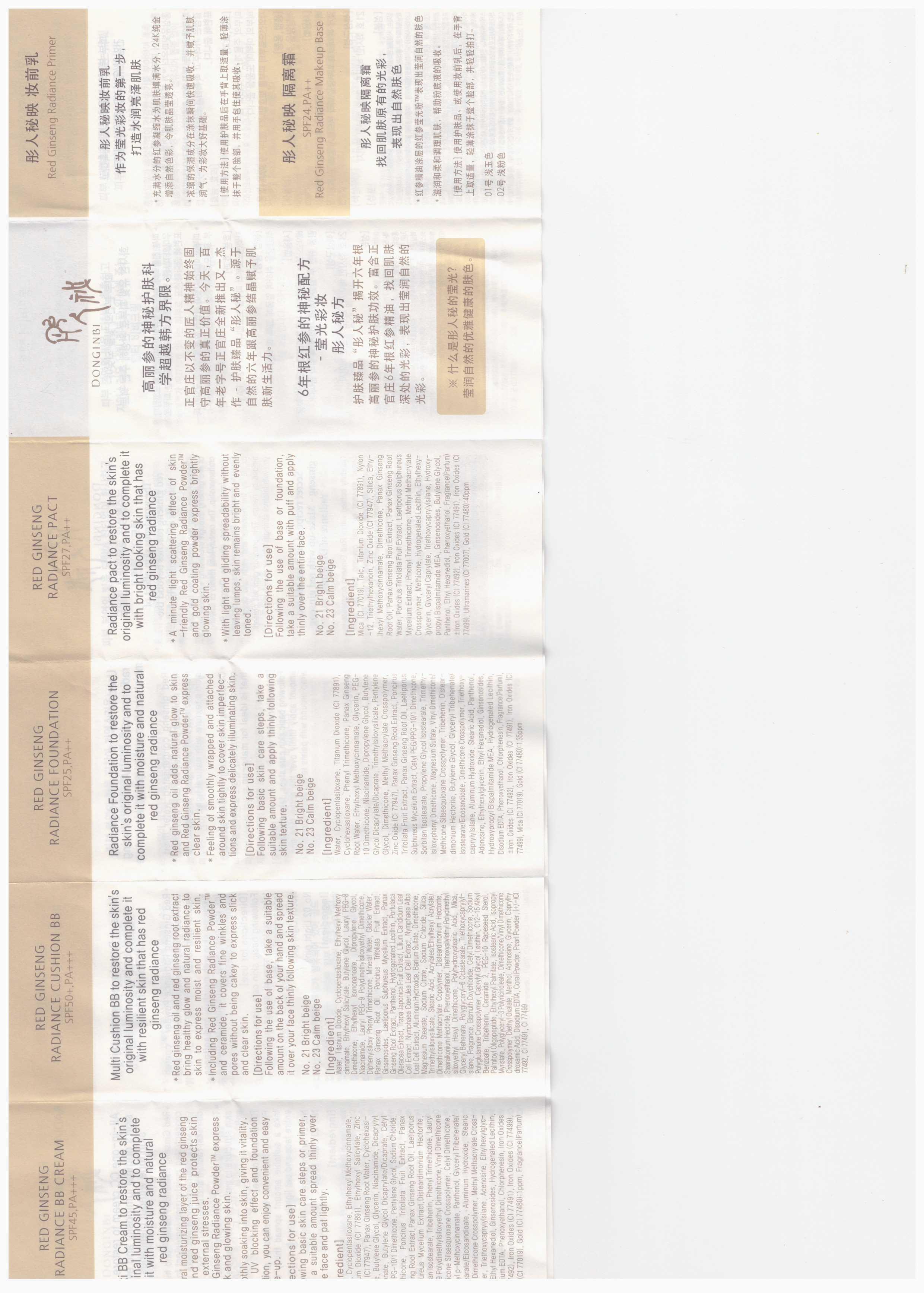 DRUG LABEL: DONGINBI RED GINSENG RADIANCE CUSHION BB 23
NDC: 69640-2001 | Form: POWDER
Manufacturer: KGC Life&Gin Co., Ltd.
Category: otc | Type: HUMAN OTC DRUG LABEL
Date: 20150308

ACTIVE INGREDIENTS: TITANIUM DIOXIDE 7 g/100 g
INACTIVE INGREDIENTS: WATER; BUTYLENE GLYCOL; GLYCERIN

Drug Facts

ACTIVE INGREDIENT

titanium dioxide

INACTIVE INGREDIENT

water, butylene glycol, glycerin, niacinamide, dipropylene glycol, iron oxides, silica, etc

PURPOSE

skin protectant

keep out of reach of the children

INDICATIONS AND USAGE

following the use of base or foundation,k take a suitable amount with puff and apply thinly over the entire face

WARNINGS

・Stop using the product when you have skin problems or the product disagrees with your skin
・Stop using the product immediately and consult a dermatologist if you have redness, swelling, itching or irritation on the skin while or after using the product.
・Don't place the product in any place where it will be subjected to extremely high or low temperatures or direct sunlight.

DOSAGE AND ADMINISTRATION

for external use only